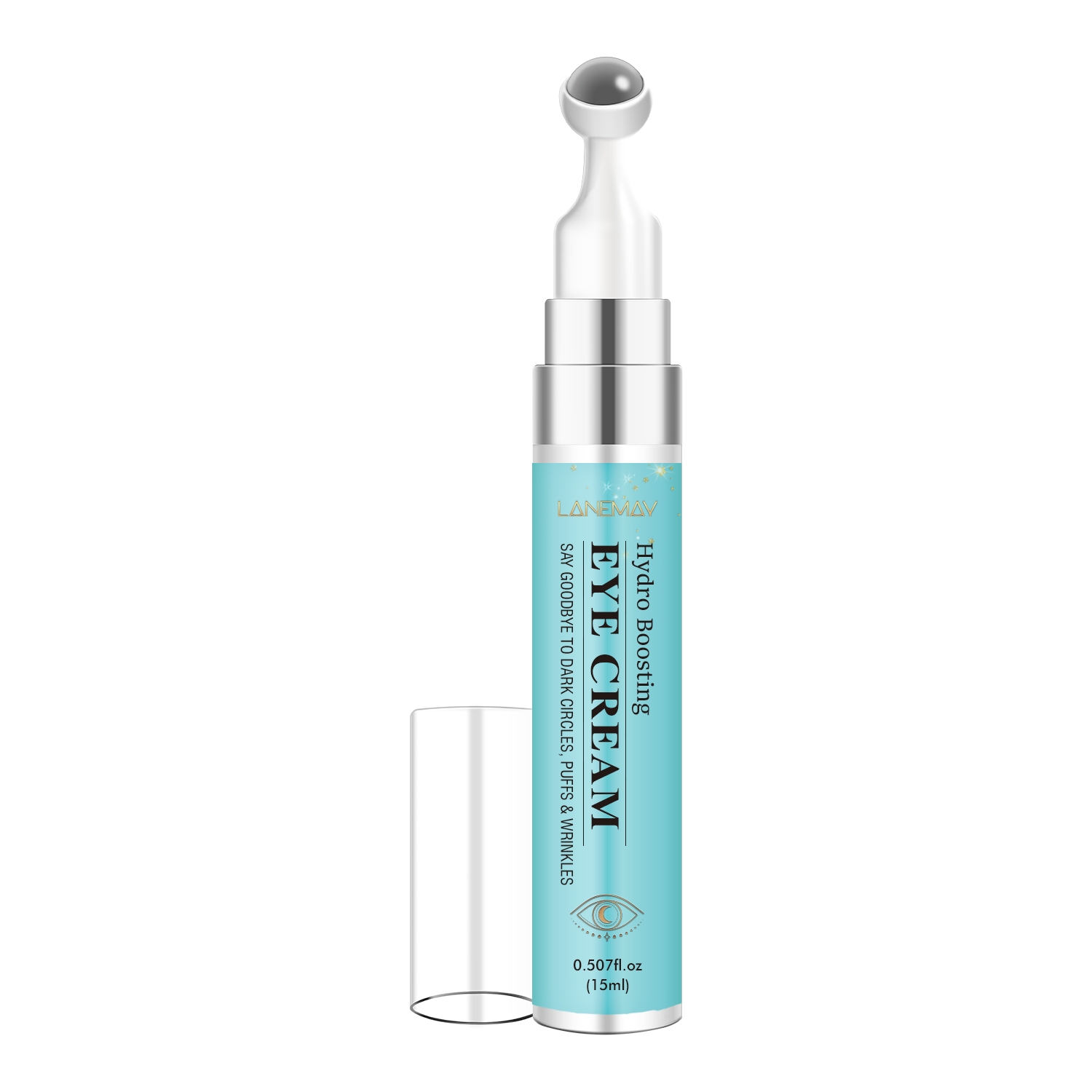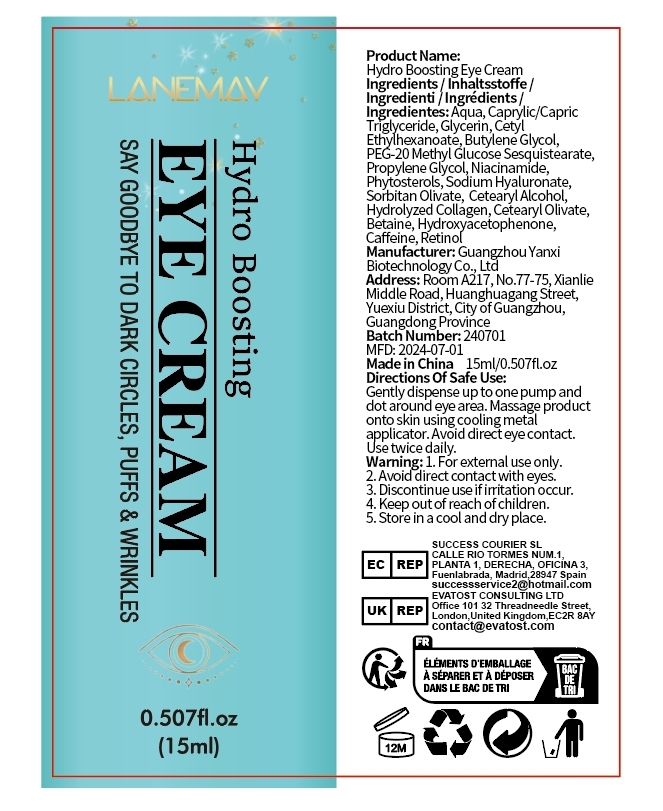 DRUG LABEL: Hydro Boosting Eye Cream
NDC: 84025-322 | Form: CREAM
Manufacturer: Guangzhou Yanxi Biotechnology Co., Ltd
Category: otc | Type: HUMAN OTC DRUG LABEL
Date: 20250123

ACTIVE INGREDIENTS: CAPRYLIC/CAPRIC TRIGLYCERIDE 3 mg/15 mL; GLYCERIN 5 mg/15 mL
INACTIVE INGREDIENTS: WATER

WARNINGS

Keep out of children

DOSAGE AND ADMINISTRATION

Gently dispense up to one pump and dot around eye area. Massage product onto skin using cooling metal applicator.Avoid direct eye contact.

INACTIVE INGREDIENT

Aqua

INDICATIONS AND USAGE

For daily skin care

Keep out of children

PURPOSE

Boosting eye skin